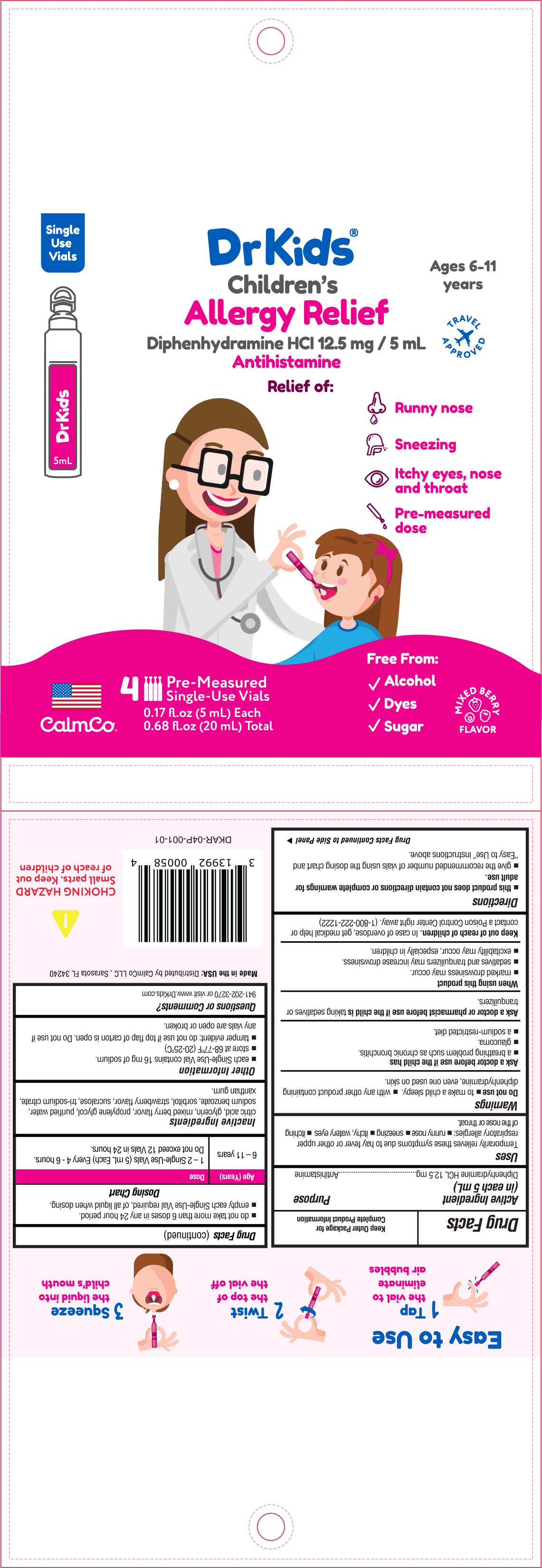 DRUG LABEL: Childrens Allergy Relief
NDC: 73282-1254 | Form: SOLUTION
Manufacturer: CalmCo LLC
Category: otc | Type: HUMAN OTC DRUG LABEL
Date: 20230724

ACTIVE INGREDIENTS: DIPHENHYDRAMINE HYDROCHLORIDE 12.5 mg/5 mL
INACTIVE INGREDIENTS: SUCRALOSE; TRISODIUM CITRATE DIHYDRATE; GLYCERIN; WATER; SORBITOL; CITRIC ACID MONOHYDRATE; XANTHAN GUM; PROPYLENE GLYCOL; SODIUM BENZOATE

DrKids Childrens Allergy Relief

Active Ingredient (in each 5mL)

Diphenhydramine HCL 12.5mg

Purpose

Antihistamine

Uses

Temporarily relieves these symptoms due to hay fever or other upper respiratory allergies: • runny nose • sneezing • itchy, watery eyes • itching of the nose or throat

Warnings

Ask a doctor before use if your child has
• a breathing problem such as chronic bronchitis
• glaucoma
• a sodium-restricted diet

Ask a doctor or pharmacist before use if the child is
taking sedatives or tranquilizers

When using this product
• marked drowsiness may occur
• sedatives and tranquilizers may increase drowsiness
• excitability may occur, especially in children

Keep out of reach of children

In case of overdose, get medical help or contact a Poison Control Center right away (1-800-222-1222)

Do not use

• to make a child sleepy • with any other product containing diphenhydramine, even one used on skin

Directions

- this product does not contain directions or complete warnings for adult use
- give the recommended number of vials below following the instructions under Easy to Use on the side panel
- do not take more than 6 doses in any 24 hour period
- empty each Single-Use Vial of all liquid when dosing

Dosing Chart

Age (Years) | Dose
6-11 Years | 1 - 2 Single-Use Vials (5mL each) every 4-6 hours. Do not exceed 12 vials in 24 hours

Inactive ingredients

citric acid, glycerin, mixed berry flavor, propylene glycol, purified water, sodium benzoate, sorbitol, strawberry flavor, sucralose, tri-sodium citrate, xanthan gum

Other information

- each Single-Use vial contains 16mg of sodium
- store at 68-77ºF (20-25ºC)
- tamper evident: do not use if top flap of carton is open. Do not use if any vials are open or broken

Questions or comments?

941-202-3270 or visit www.DrKids.com